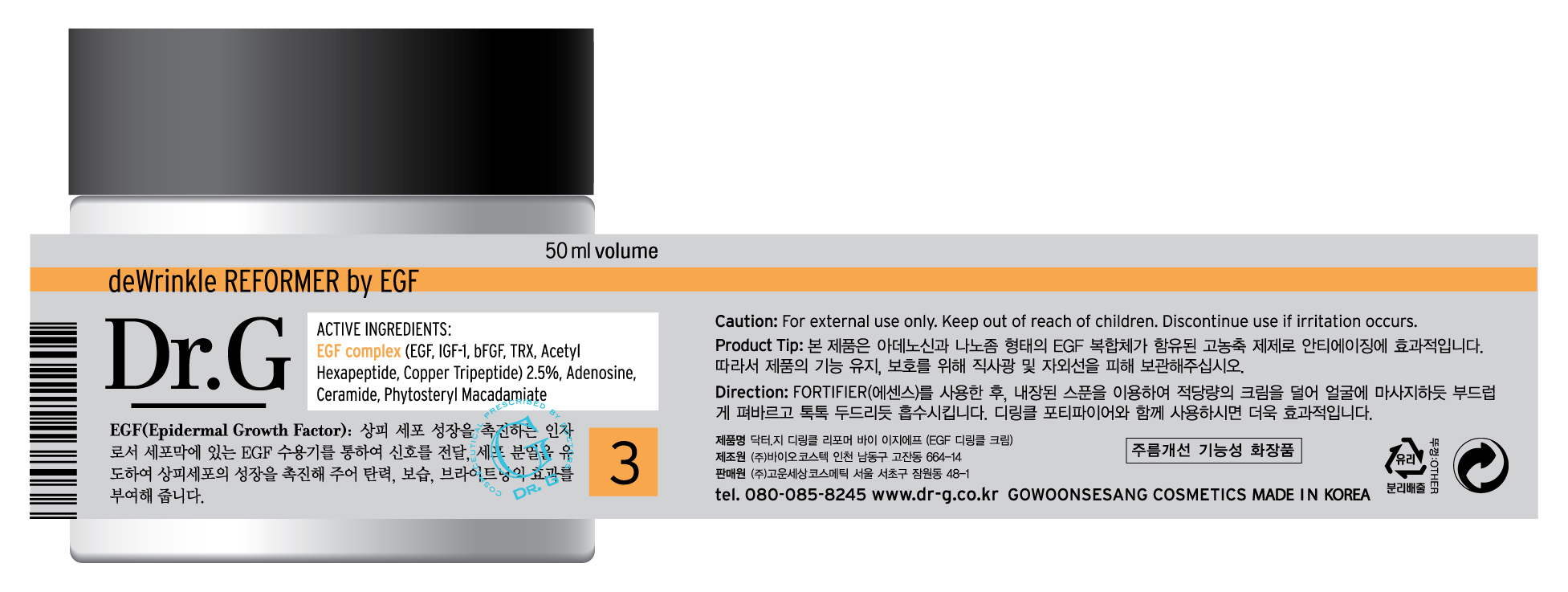 DRUG LABEL: Dr G deWrinkle REFORMER by EGF
NDC: 43948-3003 | Form: CREAM
Manufacturer: The Doctor's Cosmetic Inc
Category: otc | Type: HUMAN OTC DRUG LABEL
Date: 20091001

ACTIVE INGREDIENTS: ADENOSINE 0.02 mL/50 mL; DIMETHICONE 0.35 mL/50 mL

ACTIVE INGREDIENTS:

Dimethicone, EGF complex (EGF, IGF-1, bFGF, TRX, Acetyl Hexapeptide, Copper Tripeptide) 2.5%, Adenosine, Ceramide, Phytosteryl Macadamiate

KEEP OUT OF REACH OF CHILDREN

Caution: For external use only. Keep out of reach of children. Discontinue use if irritation occurs.

WHEN USING

DIRECTION OF USE:

After using Fortifier(essence) take an appropriate amount of cream using the enclosed spoon and gently spread on face as if massaging. Tap lightly for absorption. For better results, use with dewinkle Fortifier.

PACKAGE LABEL

Label10c